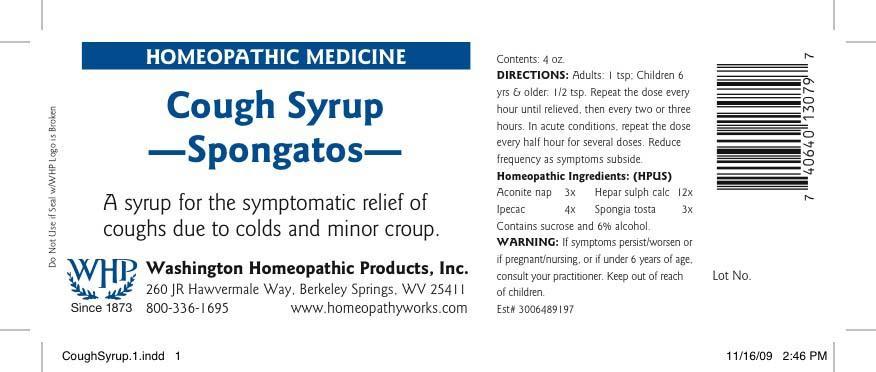 DRUG LABEL: Spongatos
NDC: 68428-001 | Form: LIQUID
Manufacturer: Washington Homeopathic Products
Category: homeopathic | Type: HUMAN OTC DRUG LABEL
Date: 20191223

ACTIVE INGREDIENTS: ACONITUM NAPELLUS 3 [hp_X]/118 mL; IPECAC 4 [hp_X]/118 mL; CALCIUM SULFIDE 12 [hp_X]/118 mL; SPONGIA OFFICINALIS SKELETON, ROASTED 3 [hp_X]/118 mL
INACTIVE INGREDIENTS: SUCROSE; ALCOHOL

DRUG FACTS

ACTIVE INGREDIENTS

CALC CARB 6C

HYDRASTIS 6C

KALI BIC 6C

USES

A syrup for the symptomatic relief of coughs due to colds and minor croup.

KEEP OUT OF REACH OF CHILDREN

Keep this and all medicines out of reach of children.

INDICATIONS

ACONITUM NAP - FEAR

HEPAR SULPH CALC - CROUPINESS

IPECAC - NAUSEA

SPONGIA TOSTA - WHEEZING

STOP USE AND ASK DOCTOR

If symptoms persist/worsen or if pregnant/nursing, stop use and consult your practitioner.

DIRECTIONS

Adults: 1 tsp;

Children 6 yrs. and older: 1/2 tsp.

Repeat the dose every hour until relieved, then every twoor three hours. In acute conditions, repeat the dose every half hour for several doses. Reduce frequency as symptoms subside.

INACTIVE INGREDIENTS

Alcohol/Lactose

PRINCIPAL DISPLAY PANEL

Enter section text here